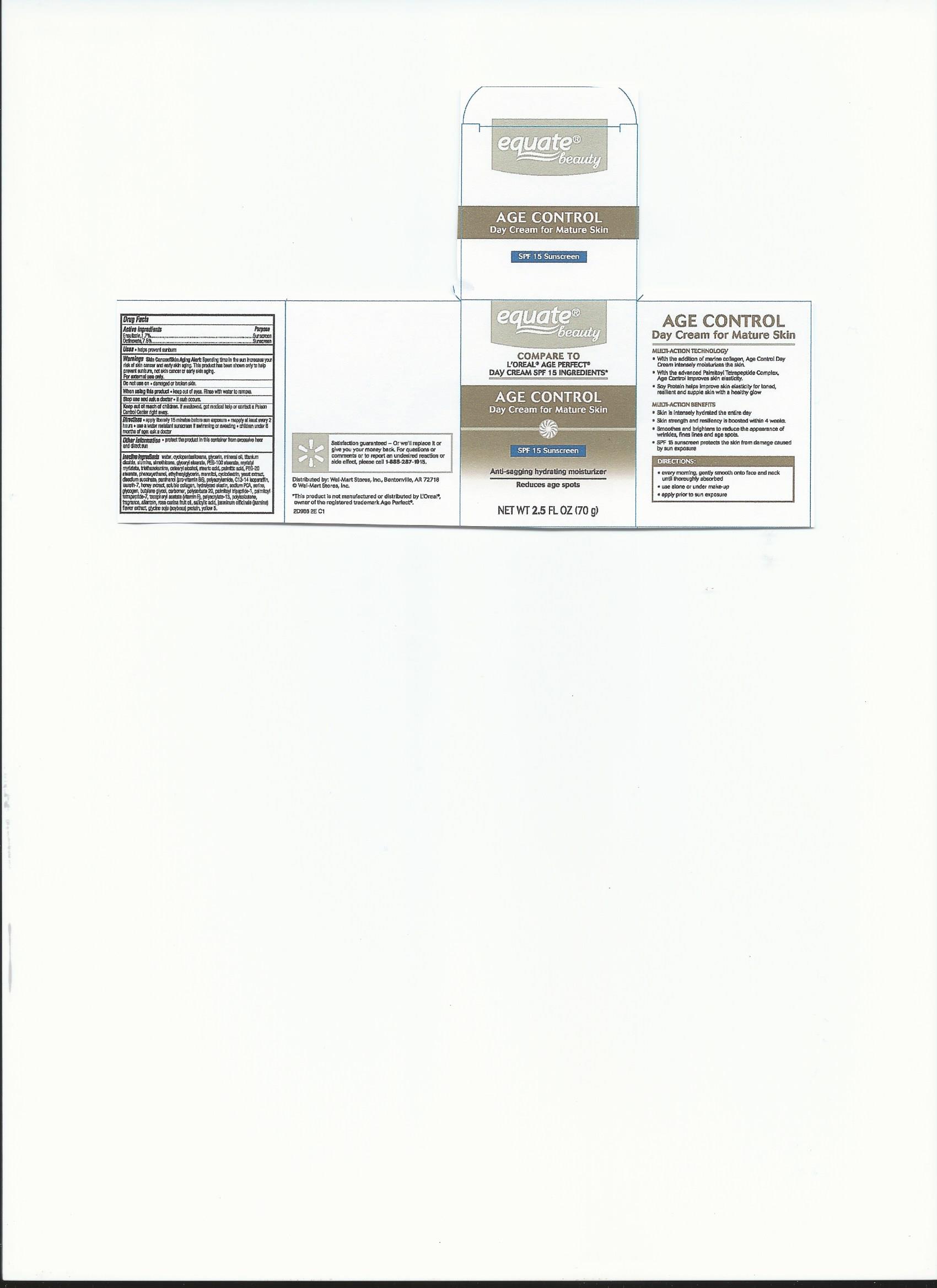 DRUG LABEL: equate beauty
NDC: 49035-877 | Form: CREAM
Manufacturer: Wal-Mart Stores, Inc.
Category: otc | Type: HUMAN OTC DRUG LABEL
Date: 20170705

ACTIVE INGREDIENTS: ENSULIZOLE 1.19 g/70 g; OCTINOXATE 5.25 g/70 g
INACTIVE INGREDIENTS: WATER; CYCLOMETHICONE 5; GLYCERIN; MINERAL OIL; TITANIUM DIOXIDE; ALUMINUM OXIDE; DIMETHICONE; GLYCERYL MONOSTEARATE; PEG-100 STEARATE; MYRISTYL MYRISTATE; TROLAMINE; CETOSTEARYL ALCOHOL; STEARIC ACID; PALMITIC ACID; PEG-20 STEARATE; PHENOXYETHANOL; ETHYLHEXYLGLYCERIN; MANNITOL; BETADEX; YEAST, UNSPECIFIED; SODIUM SUCCINATE ANHYDROUS; PANTHENOL; POLYACRYLAMIDE (1500 MW); C13-14 ISOPARAFFIN; LAURETH-7; HONEY; MARINE COLLAGEN, SOLUBLE; HYDROLYZED BOVINE ELASTIN (BASE; 1000 MW); SODIUM PYRROLIDONE CARBOXYLATE; SERINE; GLYCOGEN; BUTYLENE GLYCOL; CARBOXYPOLYMETHYLENE; POLYSORBATE 20; PALMITOYL TRIPEPTIDE-1; PALMITOYL TETRAPEPTIDE-7; .ALPHA.-TOCOPHEROL ACETATE; SODIUM POLYACRYLATE (2500000 MW); POLYISOBUTYLENE (1000 MW); ALLANTOIN; ROSA CANINA FRUIT OIL; SALICYLIC ACID; JASMINUM OFFICINALE FLOWER; SOY PROTEIN; FD&C YELLOW NO. 5

Drug Facts

Active ingredients

Ensulizone, 1.7%

Octinoxate, 7.5%

Purpose

Sunscreen

Sunscreen

INDICATIONS AND USAGE

Uses •helps prevent sunburn

WARNINGS

Warnings Skin Cancer/Skin Aging Alert: Spending time in the sun increases your

risk of skin cancer and early sking aging. This product has been shown only to help

prevent sunburn, not skin cancer or early skin aging.

For external use only.

Do not use on •damaged or broken skin

When using this product •keep out of eyes. Rinse with wter to remove.

Stop use and ask a doctor •if rash occurs.

Keep out of reach of children. If swallowed, get medical help or contact a Poison

Control Center right away.

DOSAGE AND ADMINISTRATION

Directions •apply liberally 15 minutes before sun exposure •reapply at least every 2

hours •use a water resistant sunscreen if swimming or sweating •children under 6

months of age: ask a doctor

Other information •protect the product in this container from excessive heat

and direct sun

Inactive ingredients water, cyclopentasiloxane, glycerin, mineral oil,

titanium dioxide, alumina, simethicone, glyceryl stearate, PEG-100 stearate,

myristyl myristate, triethanolamine, cetearyl alcohol, stearic acid, palmitic acid, PEG-20

stearate, phenoxyehtanol, ethylhexylglycerin, mannitol, cyclodextrin, yeast extract,

disodium succinate, panthenol (pro-vitamin B-5), polyacrylamide, C13-14 isoparaffin,

laureth-7, honey extract, soluble collagen, hydrolyzed elastin, sodium PCA, serine,

glycogen, butylene glycol, carbomer, polysorbate 20, palmitoyl tripeptide-1,

palmitoyl tripeptide-7, tocopherol acetate (vitamin E), polyacrylate-13,

polyisobutene, fragrance, allantoin, rosa canina fruit oil, salicylic acid, jasminum

officinale (jasmine) flower extract, glycine soja (soybean) protein, yellow 5